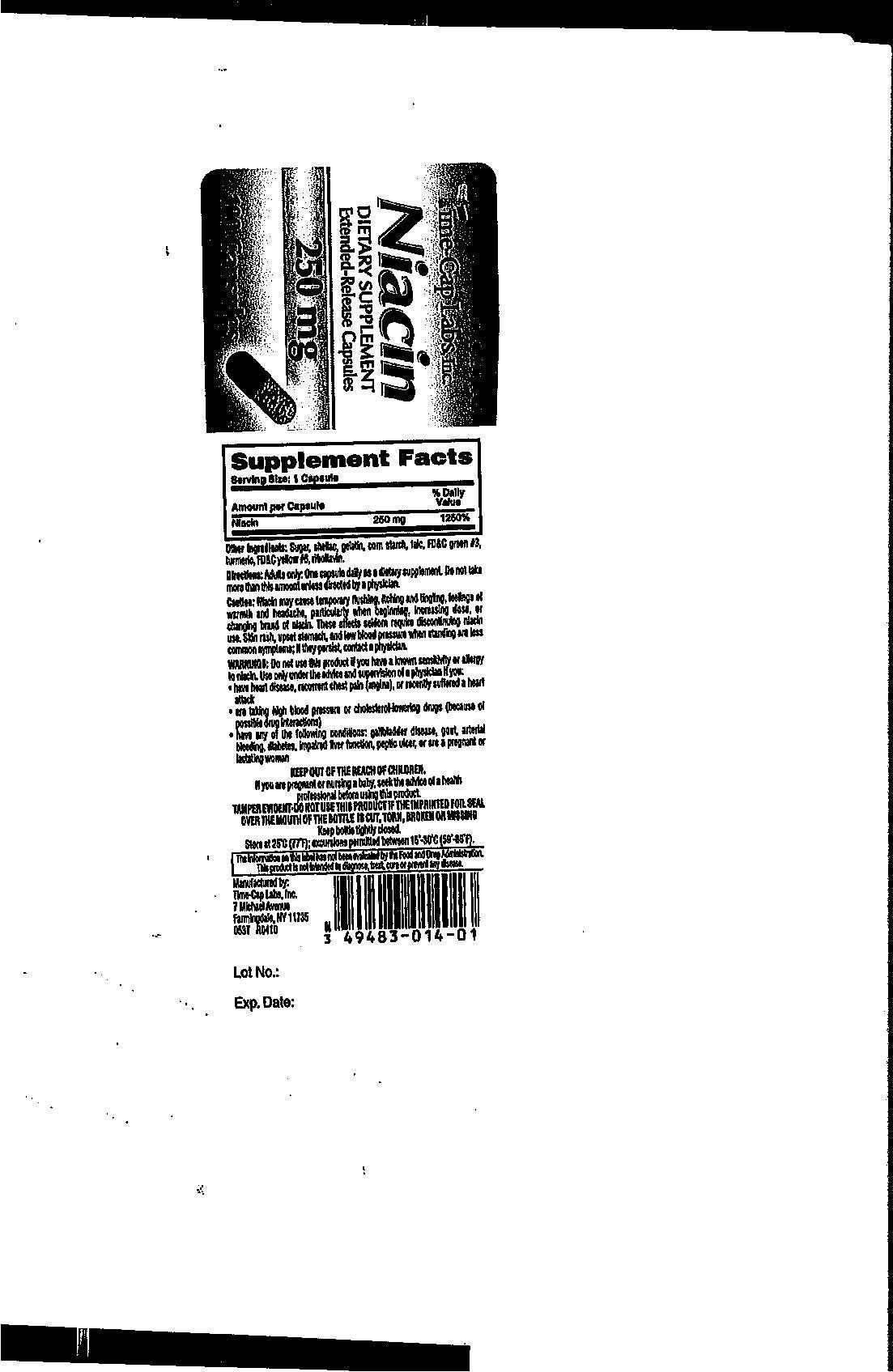 DRUG LABEL: NIACIN
NDC: 49483-014 | Form: CAPSULE, EXTENDED RELEASE
Manufacturer: TIME CAP LABS INC
Category: other | Type: DIETARY SUPPLEMENT
Date: 20140403

ACTIVE INGREDIENTS: NIACIN 250 mg/1 1
INACTIVE INGREDIENTS: SUCROSE; GELATIN; STARCH, CORN; TALC; FD&C GREEN NO. 3; TURMERIC; FD&C YELLOW NO. 6; RIBOFLAVIN

STATEMENT OF IDENTITY

Niacin Dietary Supplement Extended Release Capsules 250 mg

Do not use this product if you have a known sensitivity or allergy to niacin. Use only under the advice and supervision of a physician if you:have heart disease, abnormal chest pain (angina)or recently suffered a heart attack; are taking high blood pressure or cholestrol lowering drugs (because of possible drug interactions); have any of the following conditions: gallbladder disease, gout, arterial bleeding, diabetes, impaired liver function, peptic ulcer, or are a pregnant or lactating woman.

Keep out of Reach of children. If you are pregnant or nursing a baby, seek the advice of a health professional before using this product

HEALTH CLAIM

Dietary Supplement